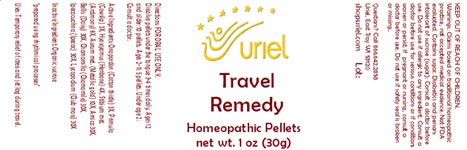 DRUG LABEL: Travel Remedy
NDC: 48951-9280 | Form: PELLET
Manufacturer: Uriel Pharmacy Inc
Category: homeopathic | Type: HUMAN OTC DRUG LABEL
Date: 20240221

ACTIVE INGREDIENTS: ONOPORDUM 3 [hp_X]/1 1; HYOSCYAMUS NIGER 4 [hp_X]/1 1; ANTIMONY 8 [hp_X]/1 1; GOLD 10 [hp_X]/1 1; ARNICA MONTANA 30 [hp_X]/1 1; BELLIS PERENNIS 30 [hp_X]/1 1; MATRICARIA RECUTITA 30 [hp_X]/1 1; IPECAC 30 [hp_X]/1 1; LYCOPODIUM CLAVATUM SPORE 30 [hp_X]/1 1; PRIMULA VERIS 3 [hp_X]/1 1
INACTIVE INGREDIENTS: SUCROSE

Travel Remedy

INDICATIONS AND USAGE

Directions: FOR ORAL USE ONLY.

DOSAGE AND ADMINISTRATION

Dissolve pellets under the tongue 3-4 times daily. Ages 12 and older: 10 pellets. Ages 2-11: 5 pellets. Under age 2: Consult a doctor.

ACTIVE INGREDIENT

Active Ingredients: Onopordon (Cotton thistle) 3X, Primula (Cowslip) 3X, Hyoscyamus (Henbane) 4X, Stibium met. (Antimony) 8X, Aurum met. (Metallic gold) 10X, Arnica 30X, Bellis (Daisy) 30X, Chamomilla (Chamomile) 30X, Ipecacuahna (Ipecac) 30X, Lycopodium (Club moss) 30X

Inactive Ingredient: Organic sucrose

"prepared using rhythmical processes"

PURPOSE

Uses: Temporary relief of stress and jet lag during travel.

KEEP OUT OF REACH OF CHILDREN.

WARNINGS

Warnings: Claims based on traditional homeopathic practice, not accepted medical evidence. Not FDA evaluated. Contains sugar. Diabetics and persons intolerant of sucrose (sugar): Consult a doctor before use. Do not use if allergic to any ingredient. Consult a doctor before use for serious conditions or if conditions worsen or persist. If pregnant or nursing, consult a doctor before use. Do not use if safety seal is broken or missing.

Questions? Call 866.642.2858
Uriel, East Troy WI 53120
shopuriel.com Lot: